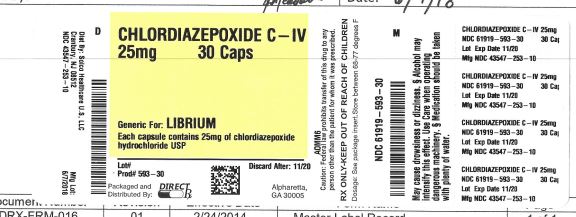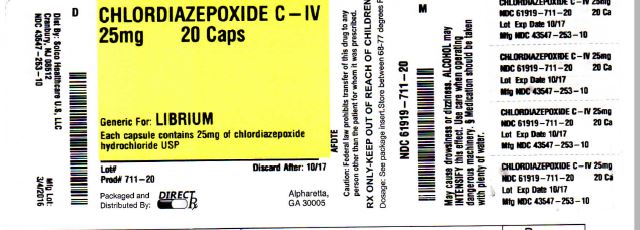 DRUG LABEL: CHLORDIAZEPOXIDE
NDC: 61919-593 | Form: CAPSULE, GELATIN COATED
Manufacturer: DIRECT RX
Category: prescription | Type: HUMAN PRESCRIPTION DRUG LABEL
Date: 20190404
DEA Schedule: CIV

ACTIVE INGREDIENTS: CHLORDIAZEPOXIDE HYDROCHLORIDE 25 mg/1 1
INACTIVE INGREDIENTS: TALC; METHYLPARABEN; PROPYLPARABEN; POTASSIUM SORBATE; D&C YELLOW NO. 10; FD&C GREEN NO. 3; TITANIUM DIOXIDE; GELATIN; STARCH, CORN; LACTOSE MONOHYDRATE

CHLORIDIAZEPOXIDE 25mg

MEDICATION GUIDE

Chlordiazepoxide Hydrochloride
Capsules, USP C-IV

What is the most important information I should know about chlordiazepoxide?

•
Chlordiazepoxide is a benzodiazepine medicine. Taking benzodiazepines with opioid medicines, alcohol, or other central nervous system depressants (including street drugs) can cause severe drowsiness, breathing problems (respiratory depression), coma and death.
•
Chlordiazepoxide can make you sleepy or dizzy, and can slow your thinking and motor skills.

o
Do not drive, operate heavy machinery, or do other dangerous activities until you know how chlordiazepoxide affects you.
o
Do not drink alcohol or take other drugs that may make you sleepy or dizzy while taking chlordiazepoxide without first talking to your healthcare provider. When taken with alcohol or drugs that cause sleepiness or dizziness, chlordiazepoxide may make your sleepiness or dizziness much worse.
o
Do not take more chlordiazepoxide than prescribed.

What is chlordiazepoxide?

•
Chlordiazepoxide is a prescription medicine used:
o
to treat anxiety disorders
o
for the short-term relief of the symptoms of anxiety
o
to treat withdrawal symptoms of acute alcoholism
o
preoperatively to treat apprehension and anxiety
•
Chlordiazepoxide is a federal controlled substance (C-IV) because it can be abused or lead to dependence. Keep chlordiazepoxide in a safe place to prevent misuse and abuse. Selling or giving away chlordiazepoxide may harm others, and is against the law. Tell your healthcare provider if you have abused or been dependent on alcohol, prescription medicines or street drugs.
•
It is not known if chlordiazepoxide is safe and effective in children under 6 years of age.
•
It is not known if chlordiazepoxide is safe and effective for use for longer than 4 months.

Do not take chlordiazepoxide if you are allergic to chlordiazepoxide or to any of the ingredients in Chlordiazepoxide Hydrochloride Capsules. See the end of this Medication Guide for a complete list of ingredients in Chlordiazepoxide Hydrochloride Capsules.

Before you take chlordiazepoxide Hydrochloride, tell your healthcare provider about all of your medical conditions, including if you:

•
have or have had depression, mood problems, or suicidal thoughts or behavior
•
have a history of drug or alcohol abuse or addiction
•
have liver or kidney problems
•
are pregnant or plan to become pregnant. Chlordiazepoxide may harm your unborn baby. You and your healthcare provider should decide if you should take chlordiazepoxide while you are pregnant
•
are breastfeeding or plan to breastfeed. Chlordiazepoxide may pass into your breast milk and may harm your baby. Talk to your healthcare provider about the best way to feed your baby if you take chlordiazepoxide .

Tell your healthcare provider about all the medicines you take, including prescription and over-the-counter medicines, vitamins, and herbal supplements.

Taking chlordiazepoxide with certain other medicines can cause side effects or affect how well chlordiazepoxide or the other medicines work. Do not start or stop other medicines without talking to your healthcare provider.

How should I take chlordiazepoxide ?

•
Take chlordiazepoxide exactly as your healthcare provider tells you to take it. Your healthcare provider will tell you how much chlordiazepoxide to take and when to take it.
•
If you take too much chlordiazepoxide, call your healthcare provider or go to the nearest hospital emergency room right away.

What should I avoid while taking chlordiazepoxide ?

•
Chlordiazepoxide can cause you to be drowsy. Do not drive a car or operate heavy machinery until you know how chlordiazepoxide affects you.
•
You should not drink alcohol while taking chlordiazepoxide. Drinking alcohol can increase your chances of having serious side effects.

What are the possible side effects of chlordiazepoxide ?

Chlordiazepoxide may cause serious side effects, including:

•
See “What is the most important information I should know about chlordiazepoxide ?”
•
Abuse and dependence. Taking chlordiazepoxide can cause physical and psychological dependence. Physical and psychological dependence is not the same as drug addiction. Your healthcare provider can tell you more about the differences between physical and psychological dependence and drug addiction.
•
Withdrawal symptoms. You may have withdrawal symptoms if you stop taking chlordiazepoxide suddenly. Withdrawal symptoms can be serious and include seizures. Mild withdrawal symptoms include a depressed mood and trouble sleeping. Talk to your healthcare provider about slowly stopping chlordiazepoxide to avoid withdrawal symptoms.

The most common side effects of chlordiazepoxide include:

•
drowsiness

•
loss of control of body movements (ataxia)

•
confusion

These are not all the possible side effects of chlordiazepoxide . Call your doctor for medical advice about side effects. You may report side effects to FDA at 1-800-FDA-1088.

How should I store Chlordiazepoxide Hydrochloride Capsules ?

•
Store Chlordiazepoxide Hydrochloride Capsules at room temperature between 68°F to 77°F (20°C to 25°C).
•
Keep Chlordiazepoxide Hydrochloride Capsules in a tightly closed container and out of the light.
•
Keep Chlordiazepoxide Hydrochloride Capsules and all medicines out of the reach of children.

General information about the safe and effective use of Chlordiazepoxide Hydrochloride Capsules.

Medicines are sometimes prescribed for purposes other than those listed in a Medication Guide. Do not use Chlordiazepoxide Hydrochloride Capsules for a condition for which it was not prescribed. Do not give Chlordiazepoxide Hydrochloride Capsules to other people, even if they have the same symptoms that you have. It may harm them. You can ask your pharmacist or healthcare provider for information about Chlordiazepoxide Hydrochloride Capsules that is written for health professionals.

What are the ingredients in Chlordiazepoxide Hydrochloride Capsules?

Active ingredient: chlordiazepoxide hydrochloride

Inactive ingredients: FD&C Yellow No. 6 plus D&C Yellow No. 10 and either FD&C Blue No. 1 or FD&C Green No. 3 , D&C Yellow No. 10 and either FD&C Blue No. 1 plus FD&C Red No. 3 or FD&C Green No. 3 plus FD&C Red No. 40 , D&C Yellow No. 10 and either FD&C Green No. 3 or FD&C Blue No. 1 (10mg only), FD&C yellow #6 (10mg only), gelatin, hydrogenated vegetable oil, lactose anhydrous, methylparaben, microcrystalline cellulose, propylparaben, silicon dioxide, sodium lauryl sulfate and titanium dioxide

Distributed by:
Solco Healthcare U.S., LLC
Cranbury, NJ 08512

This Medication Guide has been approved by the U.S. Food and Drug Administration Issued: 12/2017